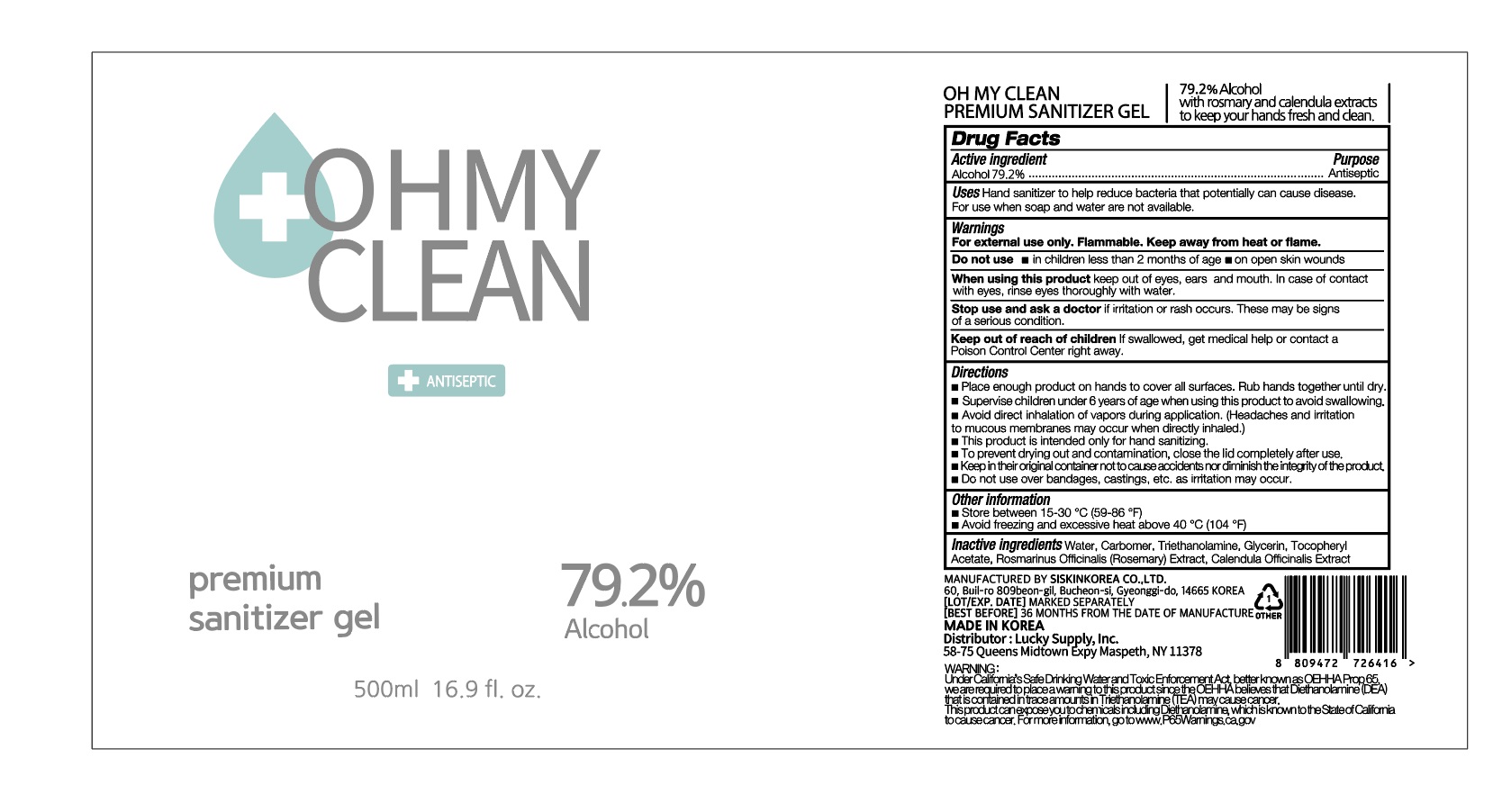 DRUG LABEL: OH MY CLEAN PREMIUM SANITIZER Gel
NDC: 74514-1792 | Form: GEL
Manufacturer: SISKINKOREA CO.,LTD.
Category: otc | Type: HUMAN OTC DRUG LABEL
Date: 20201022

ACTIVE INGREDIENTS: ALCOHOL 396 mL/500 mL
INACTIVE INGREDIENTS: GLYCERIN; .ALPHA.-TOCOPHEROL ACETATE; CALENDULA OFFICINALIS FLOWER; WATER; ROSEMARY; CARBOMER HOMOPOLYMER, UNSPECIFIED TYPE; TROLAMINE

OH MY CLEAN PREMIUM SANITIZER GEL
500 mL, 79.2 %
74514-1792-1